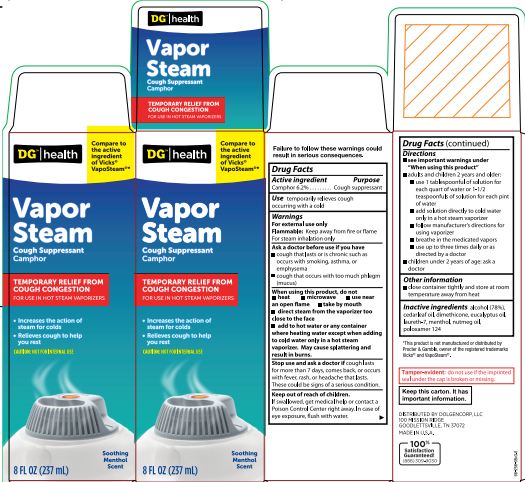 DRUG LABEL: Dollar General Vapor Steam
NDC: 55910-256 | Form: LIQUID
Manufacturer: DOLGENCORP, LLC
Category: otc | Type: HUMAN OTC DRUG LABEL
Date: 20251029

ACTIVE INGREDIENTS: CAMPHOR (SYNTHETIC) 0.623 g/10 mL
INACTIVE INGREDIENTS: ALCOHOL; CEDAR LEAF OIL; EUCALYPTUS OIL; LAURETH-7; MENTHOL; NUTMEG OIL; POLOXAMER 124; DIMETHICONE

Dollar General Medicated Vaporizing Steam Liquid

Drug Facts

Active ingredient

Camphor 6.2%

Purpose

Cough suppressant

Use

temporarily relieves cough ocurring with a cold

Warnings

For external use only.

Flammable. Keep away from fire or flame.

For steam inhalation only.

Ask a doctor before use if you have

• a cough that lasts or is chronic such as occurs with smoking, asthma, or emphysema

• cough that ocurs with too much phlegm (mucus)

When using this product, do not

- heat
- microwave
- use near an open flame
- take by mouth
- direct steam from the vaporizer too close to the face
- add to hot water or any container where heating water except when adding to cold water only in a hot steam vaporizer. May cause splattering and result in burns.

Stop use and ask a doctor if cough lasts more than 7 days, comes back, or occurs with fever, rash, or headache that lasts. These could be signs of a serious condition.

Keep out of reach of children.

If swallowed, get medical help or contact a Poison Control Center right away. In case of eye exposure, flush with water.

Directions

- see important warnings under "When using this product"
- adults & children 2 years & over:
- use 1 tablespoon of solution for each quart of water or 1½ teaspoonful of solution for each pint of water
- add solution directly to cold water only in a hot steam vaporizer
- follow manufacturer's directions for using vaporizer
- breathe in the medicated vapors
- use up to three times daily or as directed by a doctor
- children under 2 years: ask a doctor

Other information

- close container tightly and store at room temperature away from heat

Inactive ingredients

alcohol (78%), cedarleaf oil, dimethicone, eucalyptus oil, laureth-7, menthol, nutmeg oil, poloxamer 124

Tamper-evident: do not use if the imprinted seal under the cap is broken or missing.

Keep this carton. It has important information.

PRINCIPAL DISPLAY PANEL

Dollar general

Compare to the active ingredient in Vicks ® VapoSteam ®*

MEDICATED VAPORIZING STEAM LIQUID

COUGH SUPPRESSANT

CAMPHOR

Liquid Medication for Hot Steam Vaporizers

Increases the acyion of steam for colds
Relieves Cough to Help You Rest

CAUTION: NOT FOR INTERNAL USE